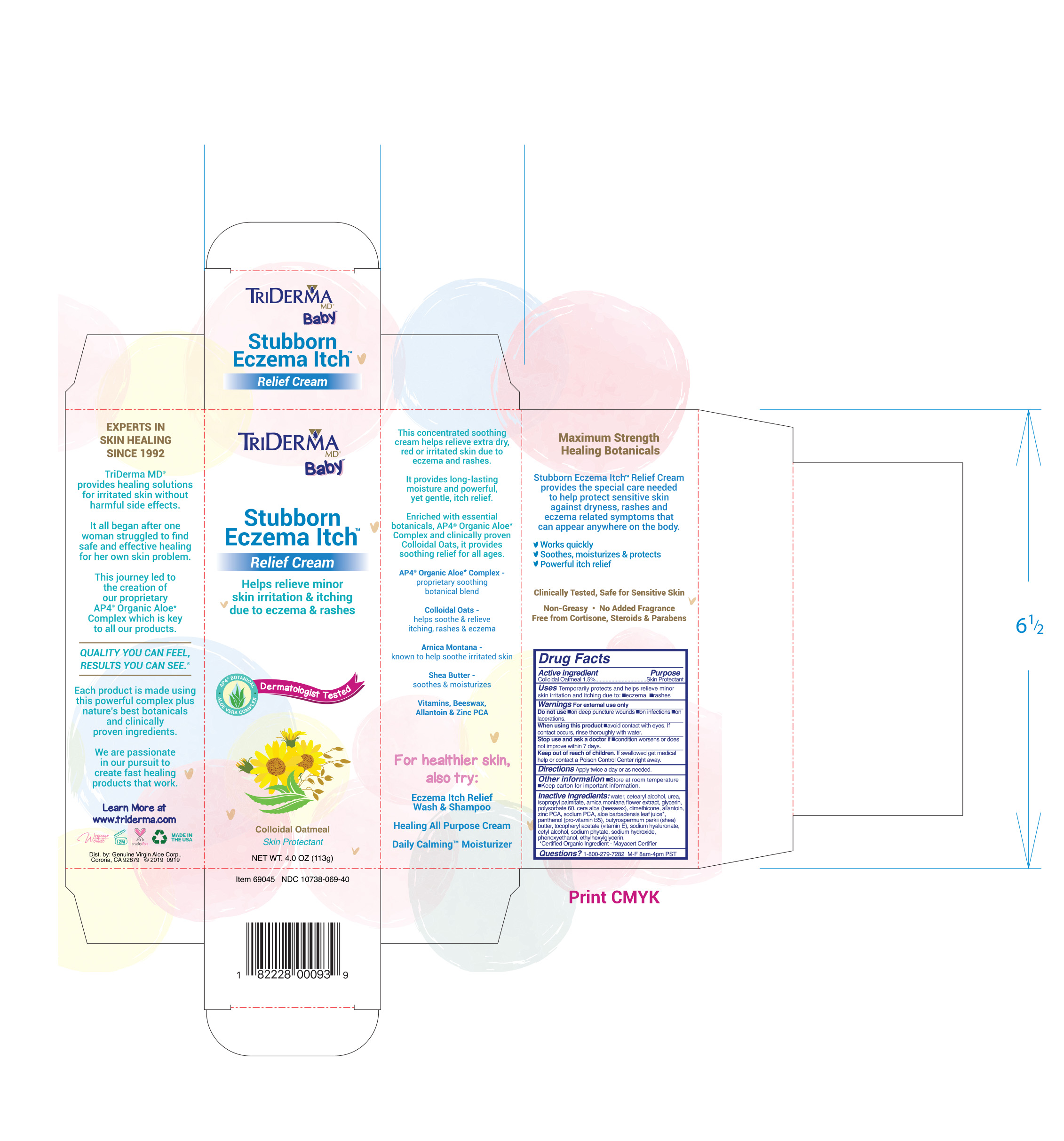 DRUG LABEL: TRIDERMA BABY STUBBORN ECZEMA ITCH RELIEF
NDC: 10738-069 | Form: CREAM
Manufacturer: Genuine Aloe Virgin Corporation
Category: otc | Type: HUMAN OTC DRUG LABEL
Date: 20260129

ACTIVE INGREDIENTS: OATMEAL 1.5 g/100 g
INACTIVE INGREDIENTS: SODIUM PCA; ZINC PCA; AVENA SATIVA (OAT) KERNEL OIL; WATER; CETOSTEARYL ALCOHOL; UREA; ISOPROPYL PALMITATE; ARNICA MONTANA FLOWER; GLYCERIN; POLYSORBATE 60; YELLOW WAX; DIMETHICONE; ALLANTOIN; ALOE VERA LEAF; PANTHENOL; SHEA BUTTER; .ALPHA.-TOCOPHEROL ACETATE; HYALURONATE SODIUM; CETYL ALCOHOL; PHYTATE SODIUM; SODIUM HYDROXIDE; PHENOXYETHANOL; ETHYLHEXYLGLYCERIN

TRIDERMA BABY STUBBORN ECZEMA ITCH RELIEF CREAM

Active ingredient

Colloidal Oatmeal 1.5%

Purpose

Skin Protectant

INDICATIONS AND USAGE

Uses temporarily protects and helps relieve minor skin irritation and itching due to: •eczema •rashes

Warnings For external use only

Do not use •on deep puncture wounds •on infections •on lacerations
When using this product •avoid contact with eyes. If contact occurs, rinse thoroughly with water.
Stop use and ask a doctor if •condition worsens or does not improve within 7 days

Keep out of reach of children. If swallowed get medical help or contact a Poison Control Center right away.

DOSAGE AND ADMINISTRATION

Directions apply twice a day or as needed.

Other information•store at room temperature •keep carton for important information.

INACTIVE INGREDIENT

Inactive ingredients: water, cetearyl alcohol, urea, isopropyl palmitate, arnica montana flower extract, glycerin, polysorbate 60, cera alba (beeswax), dimethicone, allantoin, zinc PCA, sodium PCA, aloe barbadensis leaf juice*, panthenol (pro-vitamin B5), butyrospermum parkii (shea) butter, tocopheryl acetate (vitamin E), sodium hyaluronate, cetyl alcohol, sodium phytate, sodium hydroxide, phenoxyethanol, ethylhexylglycerin.
*Certified Organic Ingredient - Mayacert Certifier

QUESTIONS

Questions? 1-800-279-7282 M-F 8am-4pm PST

Helps relieve minor skin irritation & itching due to eczema & rashes

Colloidal Oatmeal

Skin Protectant

This concentrated botanical cream helps relieve extra dry, red or irritated skin due to eczema and rashes.

It provides long-lasting moisture and powerful, yet gentle, itch relief.

Enriched with essential botanicals, AP4® Organic Aloe* Complex and clinically proven Colloidal Oats, it provides
soothing relief for all ages.

AP4® Organic Aloe* Complex - proprietary soothing botanical blend

Colloidal Oats - helps soothe & relieve itching, rashes & eczema

Arnica Montana - known to help soothe irritated skin

Shea Butter - soothes & moisturizes

Vitamins, Beeswax, Allantoin & Zinc PCA

Eczema related symptoms that can appear anywhere on the body.

- Works quickly
- Soothes, moisturizes & protects
- Powerful itch relief

Non-Greasy • No Added Fragrance
Free from Cortisone, Steroids & Parabens

EXPERTS IN SKIN HEALING SINCE 1992

TriDerma MD® provides healing solutions for irritated skin without harmful side effects.

It all began after one woman struggled to find safe and effective healing for her own skin problem.

This journey led to the creation of our proprietary AP4® Organic Aloe* Complex which is key to all our products.

QUALITY YOU CAN FEEL, RESULTS YOU CAN SEE.®

Each product is made using this powerful complex plus nature’s best botanicals and clinically proven ingredients.

We are passionate in our pursuit to create fast healing products that work.

Learn More at www.triderma.com

Mfd. by: Genuine Virgin Aloe Corp., Anaheim, CA 92807